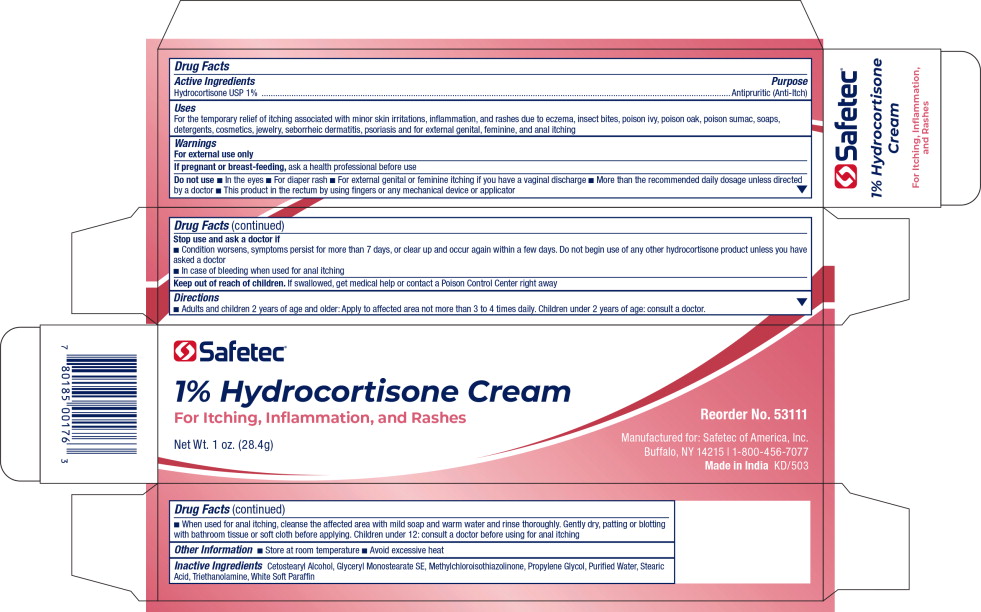 DRUG LABEL: Hydrocortisone
NDC: 61010-4402 | Form: CREAM
Manufacturer: Safetec of America, Inc.
Category: otc | Type: HUMAN OTC DRUG LABEL
Date: 20191101

ACTIVE INGREDIENTS: hydrocortisone 10 mg/1 g
INACTIVE INGREDIENTS: CETOSTEARYL ALCOHOL; GLYCERYL STEARATE SE; METHYLCHLOROISOTHIAZOLINONE; PROPYLENE GLYCOL; WATER; STEARIC ACID; TROLAMINE; PETROLATUM

Drug Facts

Active Ingredients

Hydrocortisone USP 1%

Purpose

Antipruritic (Anti-itch)

Uses

For the temporary relief of itching associated with minor skin irritations, inflammation, and rashes due to eczema, insect bites, poison ivy, poison oak, poison sumac, soaps, detergents, cosmetics, jewelry, seborrheic dermatitis, psoriasis and for external genital, feminine, and anal itching

Warnings

For external use only

PREGNANCY OR BREAST FEEDING

If pregnant or breast-feeding, ask a health professional before use

Do not use

- In the eyes
- For diaper rash
- For external genital or feminine itching if you have a vaginal discharge
- More than the recommended daily dosage unless directed by a doctor
- This product in the rectum by using fingers or any mechanical device or applicator

Stop use and ask a doctor if

- Condition worsens, symptoms persist for more than 7 days, or clear up and occur again within a few days. Do not begin use of any other hydrocortisone product unless you have asked a doctor
- In case of bleeding when used for anal itching

Keep out of reach of children. If swallowed, get medical help or contact a Poison Control Center right away

Directions

- Adults and children 2 years of age and older: Apply to affected area not more than 3 to 4 times daily. Children under 2 years of age: consult a doctor
- When used for anal itching, cleanse the affected area with mild soap and warm water and rinse thoroughly. Gently dry, patting or blotting with bathroom tissue or soft cloth before applying. Children under 12: consult a doctor before using for anal itching

Other Information

- Store at room temperature
- Avoid excessive heat

Inactive Ingredients

Cetostearyl Alcohol, Glyceryl Monostearate SE, Methylchloroisothiazolinone, Propylene Glycol, Purified Water, Stearic Acid, Triethanolamine, White Soft Paraffin

Principal Display Panel - 1 oz. Tube Label

Safetec®

1% Hydrocortisone Cream

For Itching, Inflammation, and Rashes

Net Wt. 1oz. (28.4g)

Reorder No. 53111

Manufactured for: Safetec of America, Inc.
Buffalo, NY 14215 | 1-800-456-7077
Made In India KD/503